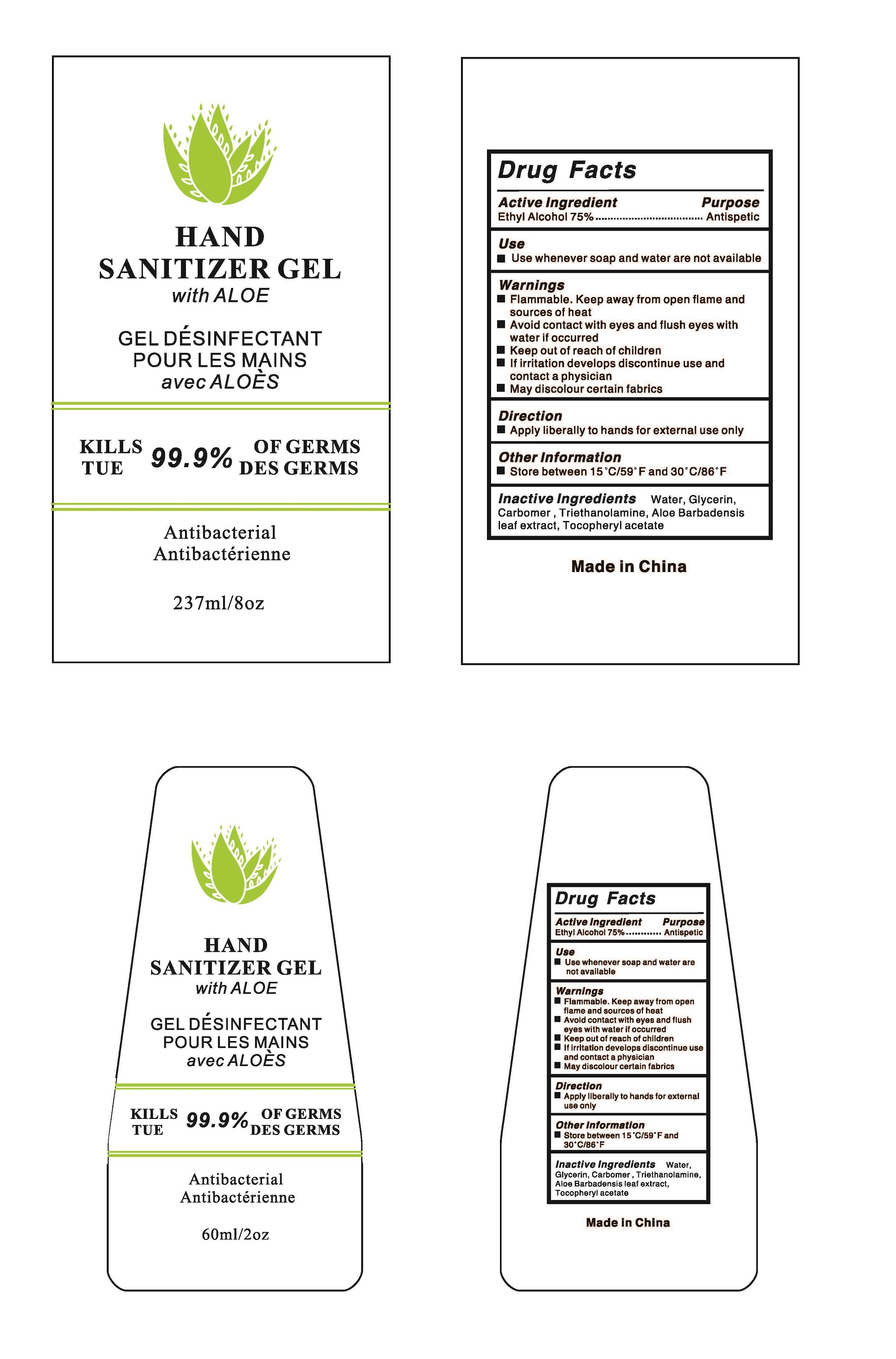 DRUG LABEL: hand sanitizer
NDC: 73788-109 | Form: GEL
Manufacturer: Hangzhou Huiji Biotechnology Co., Ltd.
Category: otc | Type: HUMAN OTC DRUG LABEL
Date: 20220224

ACTIVE INGREDIENTS: ALCOHOL 75 mL/100 mL
INACTIVE INGREDIENTS: WATER; GLYCERIN; ALOE VERA LEAF; TROLAMINE; CARBOMER 934; .ALPHA.-TOCOPHEROL ACETATE

73788-109 hand sanitizer 75% Ethyl Alcohol

Active Ingredient

Ethyl Alcohol 75%

Purpose

Antiseptic

Use

Use whenever soap and water are not available

WARNINGS

Flammable.Keep away from open flame and sources of heat
Avoid contact with eyes and flush eyes with water if occurred
Keep out of reach of children
lf irritation develops discontinue use and contact a physician
May discolour certain fabrics

keep out of reach of children

Directions

Apply liberally to hands for externaluse only

Inactive ingredients

Water, Glycerin,Carbomer , Triethanolamine, Aloe Barbadensisleaf extract,Tocopheryl acetate